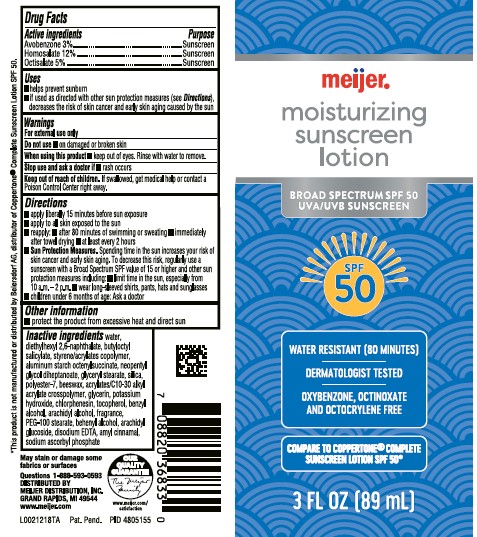 DRUG LABEL: Avobenzone, Homosalate, Octisalate
NDC: 79481-0954 | Form: LOTION
Manufacturer: Meijer, Inc.
Category: otc | Type: HUMAN OTC DRUG LABEL
Date: 20260224

ACTIVE INGREDIENTS: AVOBENZONE 30 mg/1 mL; HOMOSALATE 120 mg/1 mL; OCTISALATE 50 mg/1 mL
INACTIVE INGREDIENTS: WATER; DIETHYLHEXYL 2,6-NAPHTHALATE; BUTYLOCTYL SALICYLATE; STYRENE; BUTYL ACRYLATE/METHYL METHACRYLATE/METHACRYLIC ACID COPOLYMER (18000 MW); ALUMINUM STARCH OCTENYLSUCCINATE; NEOPENTYL GLYCOL DIHEPTANOATE; GLYCERYL MONOSTEARATE; SILICON DIOXIDE; POLYESTER-7; YELLOW WAX; CARBOMER COPOLYMER TYPE B (ALLYL PENTAERYTHRITOL CROSSLINKED); GLYCERIN; POTASSIUM HYDROXIDE; CHLORPHENESIN; TOCOPHEROL; BENZYL ALCOHOL; ARACHIDYL GLUCOSIDE; EDETATE DISODIUM ANHYDROUS; .ALPHA.-AMYLCINNAMALDEHYDE; SODIUM ASCORBYL PHOSPHATE

Meijer D54.000/D54AA
Moisturizing Sunscreen Lotion SPF 50

Active Ingredients

Avobenzone 3%

Homosalate 12%

Octisalate 5%

Purpose

Sunscreen

Uses

- helps prevent sunburn
- if used as directed with other sun protections measures (see Directions), decreases the risk of skin cancer and early skin aging caused by the sun

Warnings

For external use only

Do not use

- on damaged or broken skin

When using this product

- keep out of eyes. Rinse with water to remove.

Stop use and ask a doctor if

- rash occurs

Keep out of reach of children.

If swallowed, get medical help or contact a Poison Control Center right away.

Directions

■ apply liberally 15 minutes before sun exposure
■ apply to all skin exposed to the sun
■ reapply:
■ after 80 minutes of swimming or sweating
■ immediately after towel drying
■ at least every 2 hours
■ Sun Protection Measures.Spending time in the sun increases your risk of skin cancer and early skin aging. To decrease this risk, regularly use a sunscreen with a Broad Spectrum SPF value of 15 or higher and other sun protection measures including:
■ limit time in the sun, especially from 10 a.m.–2 p.m.
■ wear long-sleeved shirts, pants, hats and sunglasses
■ children under 6 months of age: Ask a doctor

Other information

- protect the product from excessive heat and direct sun

Inactive ingredients

water, diethylhexyl 2,6-naphthalate, butyloctyl salicylate, styrene/acrylates copolymer, aluminum starch octenylsuccinate, neopentyl glycol diheptanoate, glyceryl stearate, silica, polyester-7, beeswax, acrylates/C10-30 alkyl acrylate crosspolymer, glycerin, potassium hydroxide, chlorphenesin, tocopherol, benzyl alcohol, arachidyl alcohol, fragrance, PEG-100 stearate, behenyl alcohol, arachidyl glucoside, disodium EDTA, amyl cinnamal, sodium ascorbyl phosphate

Disclaimers

May stain or damage some fabrics or surfaces

*This product is not manufactured or distributed by Beiersdorf AG, distributor of Coppertone®Complete Sunscreen Lotion SPF 50.

Adverse Reaction

Our Quality Guraranteed

The Meijer Family

WWW.MEIJER.COM/SATISFACTION

Questions 1-888-593-0593

DISTRIBUTED BY

MEIJER DISTRIBUTION, INC.

GRAND RAPIDS, MI 49544

www.meijer.com

Principal Panel Display

meijer®

moisturizing sunscreen lotion

BROAD SPECTRUM SPF 50

UVA/UVB SUNSCREEN

SPF 50

WATER RESISTANT (80 MINUTES)

DERMATOLOGIST TESTED

OXYBENZONE, OCTINOXATE AND OCTOCRYLENE FREE

COMPARE TO COPPERTONE®COMPLETE SUNSCREEN LOTION SPF 50*

3 FL OZ (89 mL)